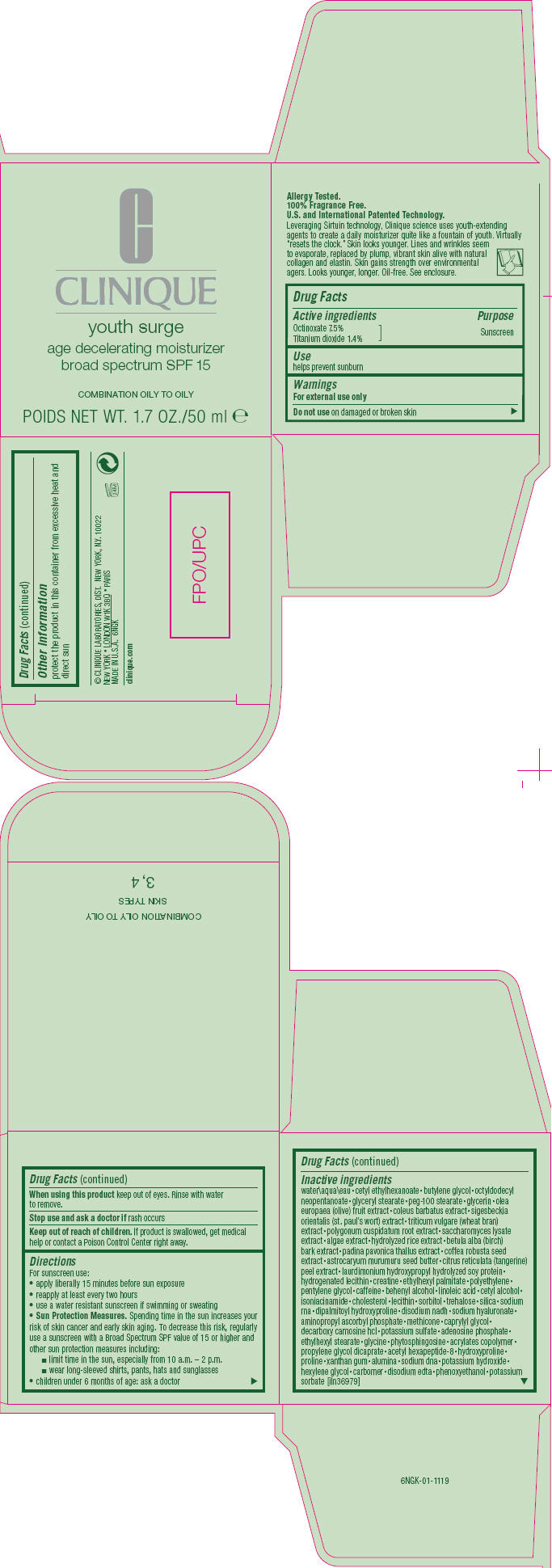 DRUG LABEL: YOUTH SURGE 
NDC: 49527-731 | Form: CREAM
Manufacturer: CLINIQUE  LABORATORIES INC.
Category: otc | Type: HUMAN OTC DRUG LABEL
Date: 20111118

ACTIVE INGREDIENTS: OCTINOXATE 7.5 mL/100 mL; TITANIUM DIOXIDE 1.4 mL/100 mL
INACTIVE INGREDIENTS: WATER; CETYL ETHYLHEXANOATE; BUTYLENE GLYCOL; OCTYLDODECYL NEOPENTANOATE; GLYCERYL MONOSTEARATE; PEG-100 STEARATE; GLYCERIN; BLACK OLIVE; PLECTRANTHUS BARBATUS ROOT; WHEAT BRAN; POLYGONUM CUSPIDATUM ROOT; SACCHAROMYCES LYSATE; BETULA PUBESCENS BARK; PADINA PAVONICA; ROBUSTA COFFEE BEAN; ASTROCARYUM MURUMURU SEED BUTTER; TANGERINE PEEL; HYDROGENATED SOYBEAN LECITHIN; CREATINE; ETHYLHEXYL PALMITATE; HIGH DENSITY POLYETHYLENE; PENTYLENE GLYCOL; CAFFEINE; DOCOSANOL; LINOLEIC ACID; CETYL ALCOHOL; ISONIACINAMIDE; CHOLESTEROL; SORBITOL; PIMAGEDINE HYDROCHLORIDE; TREHALOSE; SILICON DIOXIDE; DIPALMITOYL HYDROXYPROLINE; HYALURONATE SODIUM; AMINOPROPYL ASCORBYL PHOSPHATE; CAPRYLYL GLYCOL; POTASSIUM SULFATE; ADENOSINE PHOSPHATE; ETHYLHEXYL STEARATE; GLYCINE; PROPYLENE GLYCOL DICAPRATE; HYDROXYPROLINE; PROLINE; XANTHAN GUM; ALUMINUM OXIDE; POTASSIUM HYDROXIDE; HEXYLENE GLYCOL; EDETATE DISODIUM; PHENOXYETHANOL; POTASSIUM SORBATE

youth surge
age decelerating moisturizer
broad spectrum SPF 15

Drug Facts

Active ingredients

Octinoxate 7.5%

Titanium dioxide 1.4%

Purpose

Sunscreen

Use

helps prevent sunburn

Warnings

For external use only

Do not use on damaged or broken skin

When using this product keep out of eyes. Rinse with water to remove.

Stop use and ask a doctor if rash occurs

Keep out of reach of children. If product is swallowed, get medical help or contact a Poison Control Center right away.

Directions

For sunscreen use:

- apply liberally 15 minutes before sun exposure
- reapply at least every two hours
- use a water resistant sunscreen if swimming or sweating
- Sun Protection Measures. Spending time in the sun increases your risk of skin cancer and early skin aging. To decrease this risk, regularly use a sunscreen with a Broad Spectrum SPF value of 15 or higher and other sun protection measures including:
  - limit time in the sun, especially from 10 a.m. – 2 p.m.
  - wear long-sleeved shirts, pants, hats and sunglasses
- children under 6 months of age: ask a doctor

Inactive ingredients

water • cetyl ethylhexanoate • butylene glycol • octyldodecyl neopentanoate • glyceryl stearate • peg-100 stearate • glycerin • olea europaea (olive) fruit extract • coleus barbatus extract • sigesbeckia orientalis (st. paul's wort) extract • triticum vulgare (wheat bran) extract • polygonum cuspidatum root extract • saccharomyces lysate extract • algae extract • hydrolyzed rice extract • betula alba (birch) bark extract • padina pavonica thallus extract • coffea robusta seed extract • astrocaryum murumuru seed butter • citrus reticulata (tangerine) peel extract • laurdimonium hydroxypropyl hydrolyzed soy protein • hydrogenated lecithin • creatine • ethylhexyl palmitate • polyethylene • pentylene glycol • caffeine • behenyl alcohol • linoleic acid • cetyl alcohol • isoniacinamide • cholesterol • lecithin • sorbitol • trehalose • silica • sodium rna • dipalmitoyl hydroxyproline • disodium nadh • sodium hyaluronate • aminopropyl ascorbyl phosphate • methicone • caprylyl glycol • decarboxy carnosine hcl • potassium sulfate • adenosine phosphate • ethylhexyl stearate • glycine • phytosphingosine • acrylates copolymer • propylene glycol dicaprate • acetyl hexapeptide-8 • hydroxyproline • proline • xanthan gum • alumina • sodium dna • potassium hydroxide • hexylene glycol • carbomer • disodium edta • phenoxyethanol • potassium sorbate [iln36979]

Other information

protect the product in this container from excessive heat and direct sun

© CLINIQUE LABORATORIES, DIST. NEW YORK, N.Y. 10022

PRINCIPAL DISPLAY PANEL - 50 ml Carton

C
CLINIQUE

youth surge
age decelerating moisturizer
broad spectrum SPF 15

COMBINATION OILY TO OILY

POIDS NET WT. 1.7 OZ./50 ml e